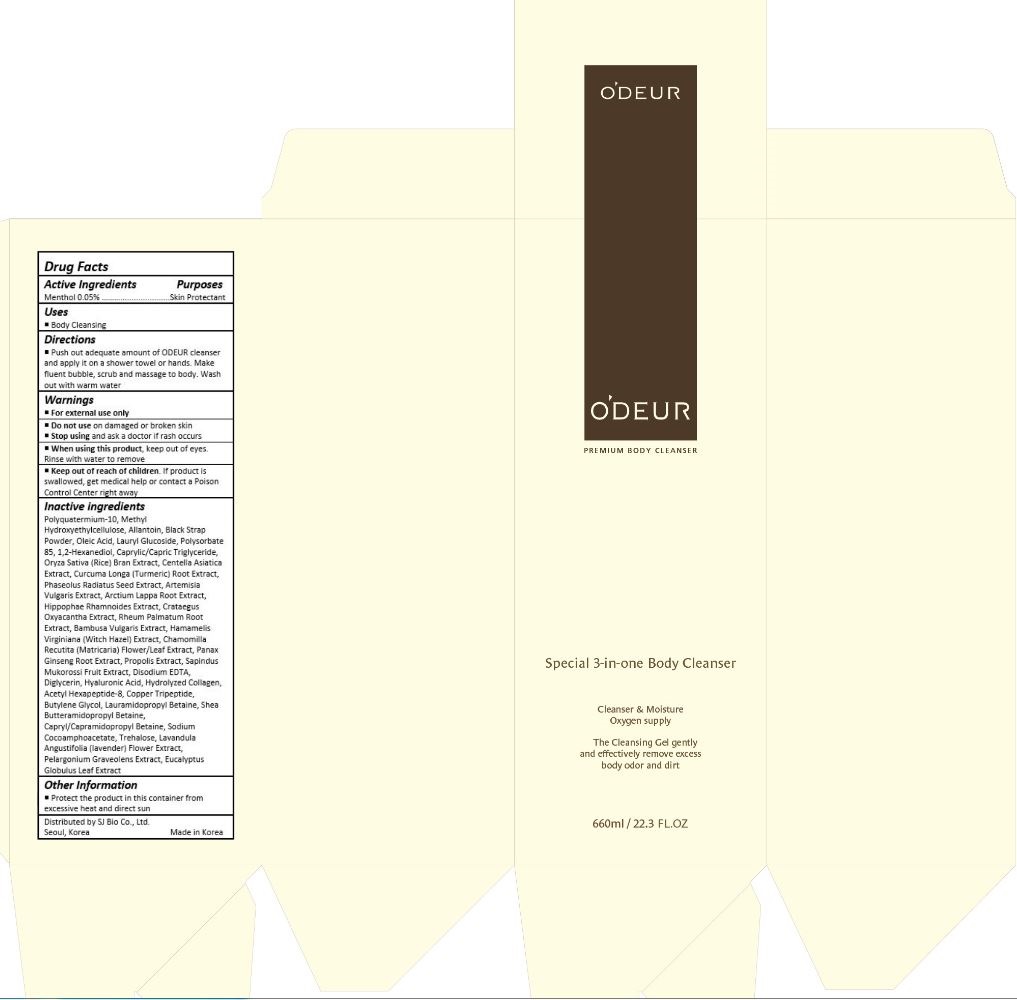 DRUG LABEL: Odeur Premium Body Cleanser
NDC: 69798-002 | Form: GEL
Manufacturer: SJ Bio Co., Ltd.
Category: otc | Type: HUMAN OTC DRUG LABEL
Date: 20250107

ACTIVE INGREDIENTS: MENTHOL, UNSPECIFIED FORM 0.33 mg/660 mL
INACTIVE INGREDIENTS: ASIAN GINSENG; PROPOLIS WAX; BUTYLENE GLYCOL; LAURAMIDOPROPYL BETAINE; CAPRYL/CAPRAMIDOPROPYL BETAINE; SODIUM COCOAMPHOACETATE; TREHALOSE; LAVANDULA ANGUSTIFOLIA FLOWER; PELARGONIUM GRAVEOLENS FLOWERING TOP; EUCALYPTUS GLOBULUS LEAF; ALLANTOIN; OLEIC ACID; LAURYL GLUCOSIDE; POLYSORBATE 85; 1,2-HEXANEDIOL; MEDIUM-CHAIN TRIGLYCERIDES; RICE BRAN; CENTELLA ASIATICA; TURMERIC; MUNG BEAN; ARTEMISIA VULGARIS ROOT; ARCTIUM LAPPA ROOT; HIPPOPHAE RHAMNOIDES FRUIT; CRATAEGUS LAEVIGATA FLOWER; RHEUM PALMATUM ROOT; BAMBUSA VULGARIS TOP; HAMAMELIS VIRGINIANA TOP; MATRICARIA RECUTITA FLOWERING TOP; SAPINDUS MUKOROSSI FRUIT; EDETATE DISODIUM; DIGLYCERIN; HYALURONIC ACID; ACETYL HEXAPEPTIDE-8; PREZATIDE COPPER

69798-002_Odeur Premium Body Cleanser

ACTIVE INGREDIENT

Menthol 0.05%

PURPOSE

Skin Protectant

INDICATIONS AND USAGE

Body Cleansing

DOSAGE AND ADMINISTRATION

Push out adequate amount of ODEUR cleanser and apply it on a shower towel or hands. Make fluent bubble, scrub and massage to body. Wash out with warm water

WARNINGS

Immediately wash off when it is in mouth or eyes.
Keep in cool place and keep away from the sun.

Keep away from infants and children.

ASK DOCTOR

Consult with doctor when there is any symptom such as erythema, swelling, irritation or sensitization.

INACTIVE INGREDIENT

Polyquatermium-10, Methyl Hydroxyethylcellulose, Allantoin, Black Strap Powder, Oleic Acid, Lauryl Glucoside, Polysorbate 85, 1,2-Hexanediol, Caprylic/Capric Triglyceride, Oryza Sativa (Rice) Bran Extract, Centella Asiatica Extract, Curcuma Longa (Turmeric) Root Extract, Phaseolus Radiatus Seed Extract, Artemisia Vulgaris Extract, Arctium Lappa Root Extract, Hippophae Rhamnoides Extract, Crataegus Oxyacantha Extract, Rheum Palmatum Root Extract, Bambusa Vulgaris Extract, Hamamelis Virginiana (Witch Hazel) Extract, Chamomilla Recutita (Matricaria) Flower/Leaf Extract, Panax Ginseng Root Extract, Propolis Extract, Sapindus Mukorossi Fruit Extract, Disodium EDTA, Diglycerin, Hyaluronic Acid, Hydrolyzed Collagen, Acetyl Hexapeptide-8, Copper Tripeptide, Butylene Glycol, Lauramidopropyl Betaine, Shea Butteramidopropyl Betaine, Capryl/Capramidopropyl Betaine, Sodium Cocoamphoacetate, Trehalose, Lavandula Angustifolia (lavender) Flower Extract, Pelargonium Graveolens Extract, Eucalyptus Globulus Leaf Extract